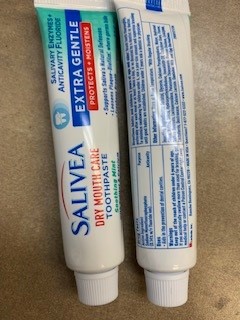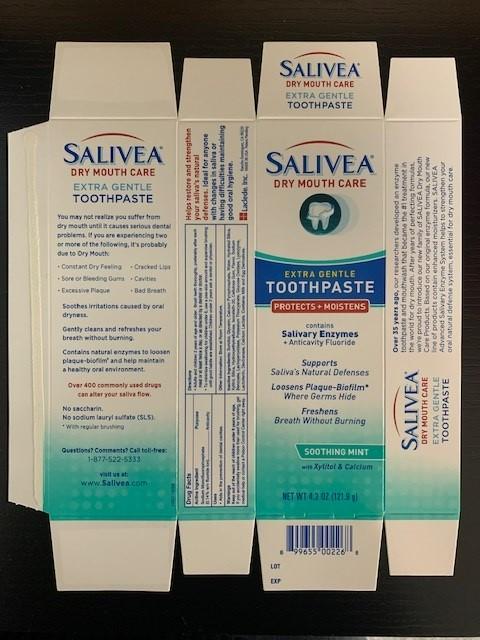 DRUG LABEL: Salivea
NDC: 54897-701 | Form: PASTE, DENTIFRICE
Manufacturer: Laclede, Inc.
Category: otc | Type: HUMAN OTC DRUG LABEL
Date: 20260213

ACTIVE INGREDIENTS: SODIUM MONOFLUOROPHOSPHATE 1.4 mg/1 g
INACTIVE INGREDIENTS: SORBITOL; GLYCERIN; CALCIUM PYROPHOSPHATE; WATER; HYDRATED SILICA; XYLITOL; SILICON DIOXIDE; HYDROXYETHYL CELLULOSE (140 MPA.S AT 5%); ISOCETETH-20; CARBOXYMETHYLCELLULOSE SODIUM; MINT; SODIUM BENZOATE; LACTOPEROXIDASE BOVINE; POTASSIUM THIOCYANATE; GLUCOSE OXIDASE; LYSOZYME; LACTOFERRIN, BOVINE; DEXTRANASE PENICILLIUM; CALCIUM LACTATE

ACTIVE INGREDIENT

Sodium Monofluorophosphate (0.14% w/v fluoride ion)

PURPOSE

Anticavity

USES

Aids in the prevention of dental cavities.

WARNINGS

Keep out of the reach of children under 6 years of age.

If you accidentally swallow more than used for brushing, get medical help or contact a Poison Control Center right away.

KEEP OUT OF REACH OF CHILDREN

Keep out of the reach of children under 6 years of age.

DIRECTIONS

- Adults and children 2 years of age and older: Brush teeth thoroughly, preferably after each meal or at least twice a day, or as directed by a dentist or doctor.
- To minimize swallowing for children under 6, use a pea-size amount and supervise brushing until good habits are established. Children under 2 years ask a dentist or physician.

OTHER INFORMATION

Store at Room Temperature.

INACTIVE INGREDIENTS

Sorbitol, Glycerin, Calcium Pyrophosphate, Water, Hydrated Silica, Xylitol, Silica, Hydroxyethylcellulose, Isoceteth-20, Cellulose Gum, Flavor, Sodium Benzoate, Lactoperoxidase, Potassium Thiocyanate, Glucose Oxidase, Lysozyme, Lactoferrin, Dextranase, Calcium Lactate.

QUESTIONS

Questions? Comments? Call toll-free: 1-877-522-5333

PACKAGE LABEL.PRINCIPAL DISPLAY PANEL

SALIVEA DRY MOUTH CARE TOOTHPASTE

Soothing Mint

with Xylitol & Calcium